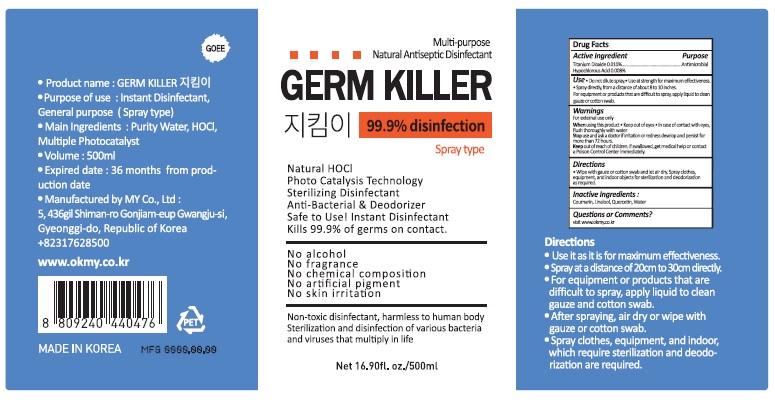 DRUG LABEL: JIKIMI GERM KILLER-Spray
NDC: 71544-0014 | Form: LIQUID
Manufacturer: MY Corp.,Ltd
Category: otc | Type: HUMAN OTC DRUG LABEL
Date: 20200728

ACTIVE INGREDIENTS: TITANIUM DIOXIDE 0.05 g/500 mL; HYPOCHLOROUS ACID 0.04 g/500 mL
INACTIVE INGREDIENTS: COUMARIN; LINALOOL, (+)-; QUERCETIN; WATER

MY Corp - JIKIMI GERM KILLER

ACTIVE INGREDIENT

titanium dioxide, hypochlorous acid

INACTIVE INGREDIENT

Coumarin, Linalool, Quercetin, Water

PURPOSE

- Do not dilute spray
- Use at strength for maximum effectiveness
- Spray directly, from a distance of about 8 to 10 inches. For equipment or products that are difficult to spray, apply liquid to clean gauze or cotton swab.

keep out of reach of the children

INDICATIONS AND USAGE

- Wipe with gauze or cotton swab and let air dry. Spray clothes, equipment, and indoor objects for sterilization and deodorization as required.

WARNINGS

For external use only.

When using this product keep out of eyes, ears, and mouth. In case of contact with eyes, rinse thoroughly with water.

Stop use and ask a doctor if irritation or rash occurs develop and persist for more than 72 hours.

Keep out of reach of children. If swallowed, get medical help or contact a Poison Control Center right away.

DOSAGE AND ADMINISTRATION

for external use only